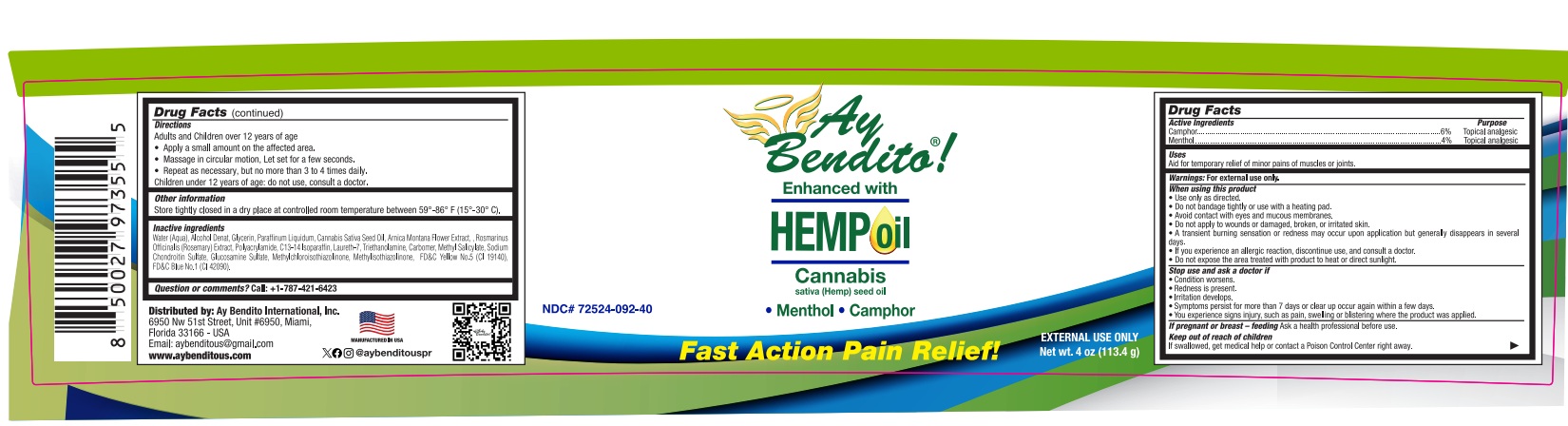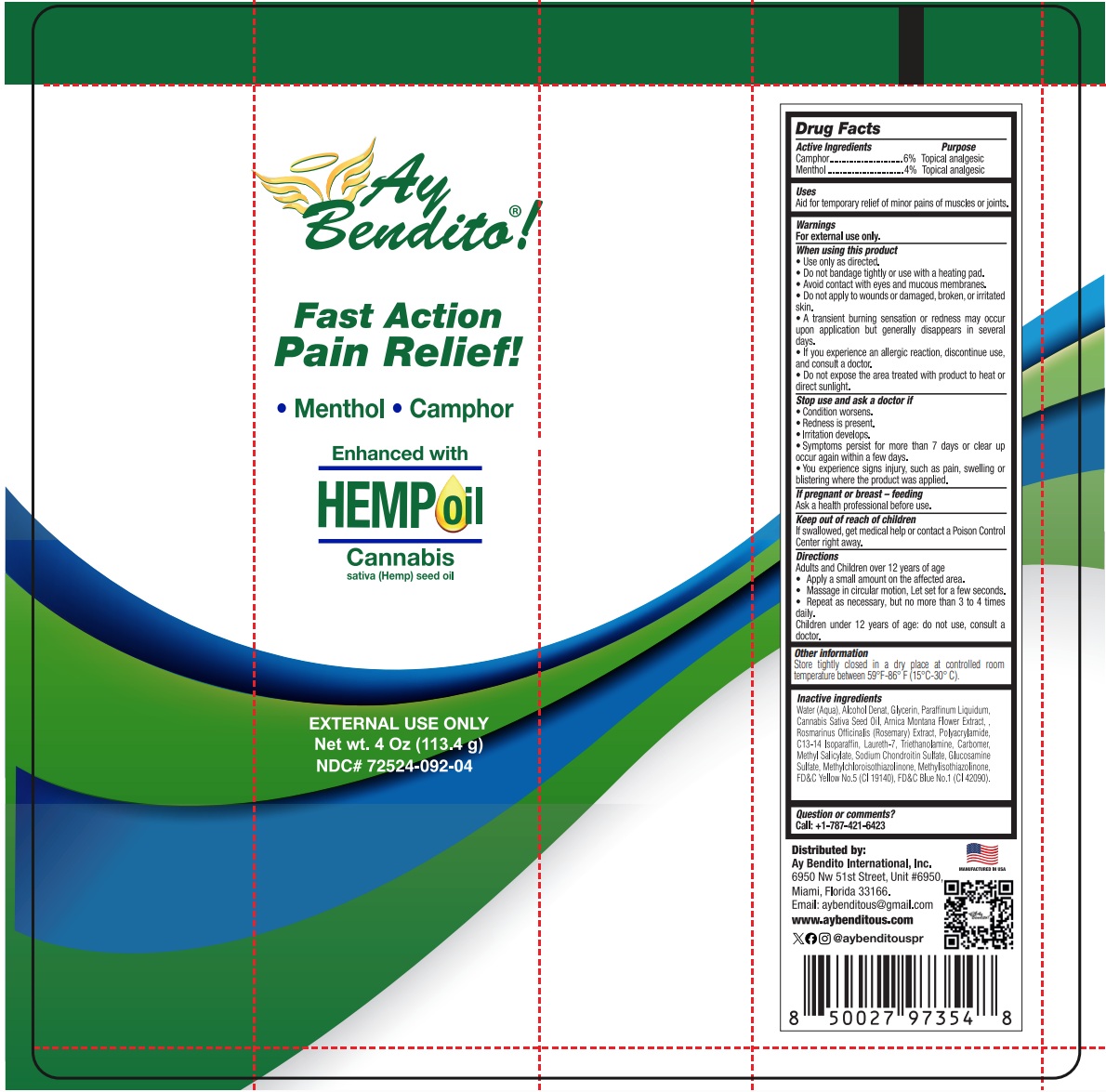 DRUG LABEL: AY BENDITO HEMP
NDC: 72524-092 | Form: GEL
Manufacturer: AY BENDITO INTERNATIONAL, INC
Category: otc | Type: HUMAN OTC DRUG LABEL
Date: 20251208

ACTIVE INGREDIENTS: CAMPHOR (SYNTHETIC) 6 g/100 g; MENTHOL 4 g/100 g
INACTIVE INGREDIENTS: METHYLCHLOROISOTHIAZOLINONE; METHYLISOTHIAZOLINONE; FD&C BLUE NO. 1; POLYSORBATE 20; METHYL SALICYLATE; ROSMARINUS OFFICINALIS WHOLE; CARBOMER 940; MINERAL OIL; FD&C YELLOW NO. 5; ALCOHOL; CANNABIS SATIVA SEED OIL; C13-14 ISOPARAFFIN; LAURETH-7; TROLAMINE; GLUCOSAMINE SULFATE; WATER; GLYCERIN; ARNICA MONTANA FLOWER; SODIUM CHONDROITIN SULFATE (PORCINE; 5500 MW)

72524-092-04
72524-092-40

ACTIVE INGREDIENT

Camphor ………………. 6%

Menthol …………….…. 4%

PURPOSE

Topical Analgesic

INDICATIONS AND USAGE

Aid for temporary local relief of minor pain in muscles or joints.

WARNINGS

For external use only.

WHEN USING

- Use only as directed
- Do not bandage tightly or use with a heating pad
- Avoid contact with eyes and mucous membranes
- Do not apply to wounds or damaged, broken or irritated skin
- A transient burning sensation or redness may occur upon application but generally disappears in several days
- If you experience an allergic reaction, discontinue use and consult a doctor
- Do not expose the area treated with product to heat or direct sunlight.

STOP USE

- Condition worsens
- Redness is present
- Irritation develops
- Symptoms persist for more than 7 days or clear up occur again within a few days
- You experience signs injury, such as pain, swelling or blistering where the product was applied.

If pregnant or breast – feeding

Ask a health professional before use.

KEEP OUT OF REACH OF CHILDREN

If swallowed, get medical help or contact a Poison Control Center right away.

DIRECTIONS

Adults and Children over 12 years of age:

Apply a small amount on the affected area.
Massage in circular motion, let set for a few seconds.
Repeat as necessary, but no more than 3 to 4 times daily.
Children under 12 years of age: do not use, consult a doctor.

OTHER INFORMATION

Store tightly closed in a dry place at controlled room temperature between 59°-86° F (15°-30° C).

INACTIVE INGREDIENT

Water (Aqua), Alcohol Denat, Glycerin, Paraffinum Liquidum, Cannabis Sativa Seed Oil, Arnica Montana Flower Extract, , Rosmarinus Officinalis (Rosemary) Extract, Polyacrylamide, C13-14 Isoparaffin, Laureth-7, Triethanolamine, Carbomer, Methyl Salicylate, Sodium Chondroitin Sulfate, Glucosamine Sulfate Methylchloroisothiazolinone, Methylisothiazolinone, FD&C Yellow No.5 (CI 19140), FD&C Blue No.1 (CI 42090).

QUESTION OR COMMENTS?

Call: +1-787-421-6423